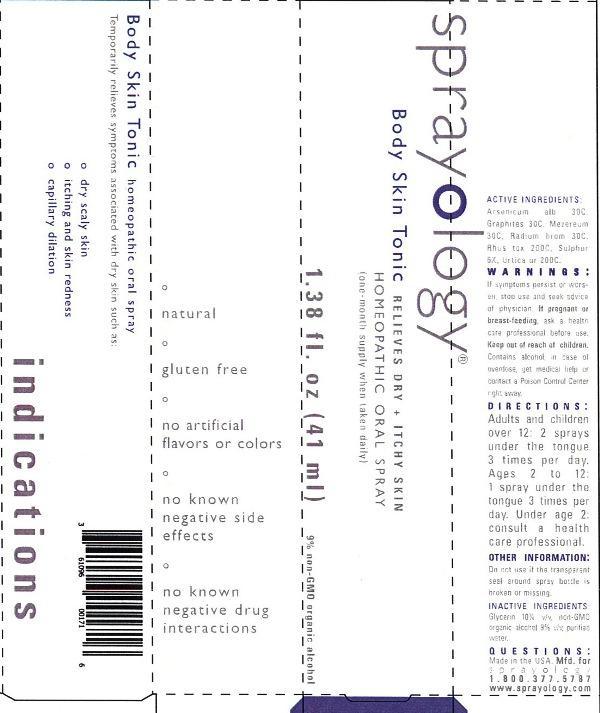 DRUG LABEL: Sprayology Body Skin Tonic
NDC: 61096-0017 | Form: LIQUID
Manufacturer: Eight and Company
Category: homeopathic | Type: HUMAN OTC DRUG LABEL
Date: 20140205

ACTIVE INGREDIENTS: ARSENIC TRIOXIDE 30 [hp_C]/41 mL; GRAPHITE 30 [hp_C]/41 mL; DAPHNE MEZEREUM BARK 30 [arb'U]/41 mL; RADIUM BROMIDE 30 [hp_C]/41 mL; TOXICODENDRON PUBESCENS LEAF 200 [hp_C]/41 mL; SULFUR 6 [hp_C]/41 mL; URTICA URENS 200 [hp_C]/41 mL
INACTIVE INGREDIENTS: GLYCERIN; ALCOHOL; WATER

Sprayology Body Skin Tonic

ACTIVE INGREDIENT

Active Ingredients: Arsenicum album 30C, Graphites 30C, Mezereum 30C, Radium bromatum 30C, Rhus toxicodendron 200C, Sulphur 6X, Urtica urens 200C.

WARNINGS

Warnings: If symptoms persist or worsen, stop use and seek advice of physician. If pregnant or breast-feeding, ask a health care professional before use. Keep out of reach of children. Contains alcohol, in case of overdose, get medical help or contact a Poison Control Center right away.

Keep out of reach of children.

PURPOSE

Temporarily relieves symptoms associated with dry skin such as:

- dry scaly skin
- itching and skin redness
- capillary dilation

Directions:

- Adults and children over 12: 2 sprays under the tongue 3 times per day.
- Ages 2 to 12: 1 spray under the tongue 3 times per day.
- Under age 2: consult a health care professional.

Other Information: Do not use if the transparent seal around spray bottle is broken or missing.

INACTIVE INGREDIENT

Inactive Ingredients: Glycerin 10% v/v, non-GMO organic alcohol 9% v/v, purified water.

INDICATIONS AND USAGE

Temporarily relieves symptoms associated with dry skin such as:

° dry scaly skin

° itching and skin redness

° capillary dilation

° natural

° gluten free

° no artificial flavors or colors

° no known negative side effects

° no known negative drug interactions